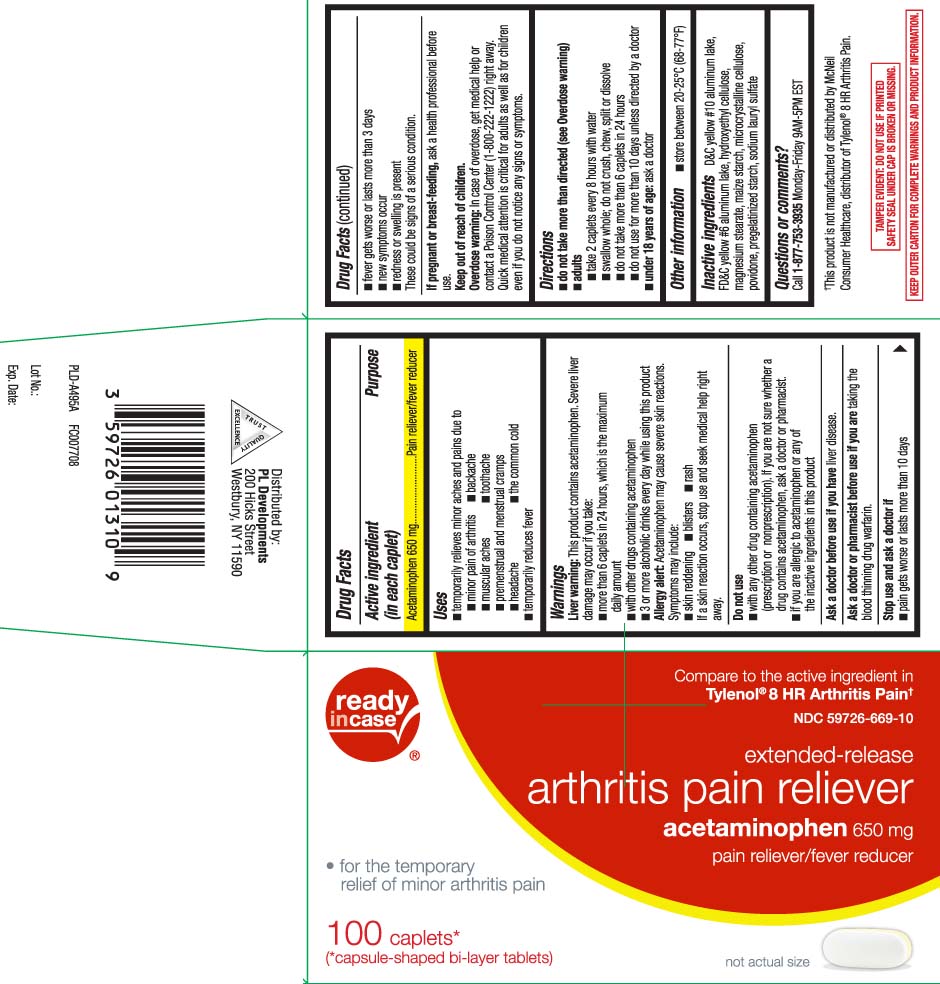 DRUG LABEL: ArthritisPain Relief
NDC: 59726-669 | Form: TABLET
Manufacturer: P & L Development, LLC
Category: otc | Type: HUMAN OTC DRUG LABEL
Date: 20241101

ACTIVE INGREDIENTS: ACETAMINOPHEN 650 mg/1 1
INACTIVE INGREDIENTS: D&C YELLOW NO. 10 ALUMINUM LAKE; FD&C YELLOW NO. 6; HYDROXYETHYL CELLULOSE (140 MPA.S AT 5%); MAGNESIUM STEARATE; STARCH, CORN; MICROCRYSTALLINE CELLULOSE; POVIDONE; SODIUM STARCH GLYCOLATE TYPE A CORN; SODIUM LAURYL SULFATE

Drug Facts

Active ingredient (in each caplet)

Acetaminophen 650 mg

Purpose

Pain reliever/fever reducer

Uses

- temporarily relieves minor aches and pains due to:
  - minor pain of arthritis
  - backache
  - muscular aches
  - toothache
  - premenstrual and menstrual cramps
  - headache
  - the common cold
- temporarily reduces fever

Warnings

Liver warning: This product contains acetaminophen. Severe liver damage may occur if you take:

- more than 6 caplets in 24 hours, which is the maximum daily amount
- with other drugs containing acetaminophen
- 3 or more alcoholic drinks ever day while using this product

Allergy alert: Acetaminophen may cause severe skin reactions. Symptoms may include:

- skin reddening
- blisters
- rash

If a skin reaction occurs, stop use and seek a medical help right away.

Do not use

- with any other drug containing acetaminophen (prescription or nonprescription). If you are not sure whether a drug contains acetaminophen, ask a doctor or pharmacist.
- if you are allergic to acetaminophen or any of the inactive ingredients in this product

Ask a doctor before use if you have

liver disease.

Ask a doctor or pharmacist before use if you are

taking the blood thinning drug warfarin.

Stop use and ask a doctor if

- pain gets worse or lasts more than 10 days
- fever gets worse or lasts more than 3 days
- new symptoms occur
- redness or swelling is present

These could be signs of a serious condition.

If pregnant or breast-feeding,

ask a health professional before use.

Keep out of reach of children.

Overdose warning: In case of overdose, get medical help or contact a Poison Control Center (1-800-222-1222) right away. Quick medical attention is critical for adults as well as for children even if you do not notice any signs or symptoms.

Directions

- do not take more than directed (see Overdose warning)
- adults
  - take 2 caplets every 8 hours with water
  - swallow whole; do not crush, chew, split or dissolve
  - do not take more than 6 caplets in 24 hours
  - do not use for more than 10 days unless directed by a doctor
- under 18 years of age: ask a doctor

Other information

- store between 20-25°C (68-77°F)

Inactive ingredients

D&C yellow #10 aluminum lake, FD&C yellow #6 aluminum lake, hydroxyethyl cellulose, magnesium stearate, maize starch, microcrystalline cellulose, povidone, pregelatinized starch, sodium lauryl sulfate

Questions or comments?

Call 1-877-753-3935 Monday-Friday 9AM-5PM EST

Principal Display Panel

Compare to the active ingredient of Tylenol® 8HR Arthritis Pain†

extended-release

arthritis pain reliever

acetaminophen 650 mg

pain reliever/fever reducer

- for the temporary relief of minor arthritis pain

caplets*

(*capsule-shaped bi-layer tablets)

†This product is not manufactured or distributed by McNeil Consumer Healthcare, distributor of Tylenol® 8 HR Arthritis Pain.

TAMPER EVIDENT: DO NOT USE IF PRINTED SAFETY SEAL UNDER CAP IS BROKEN OR MISSING.

KEEP OUTER CARTON FOR COMPLETE WARNINGS AND PRODUCT INFORMATION.

Distributed by:

PL Developments

200 Hicks Street

Westbury, NY 11590

Product Label

READYinCASE Arthritis Pain Reliever